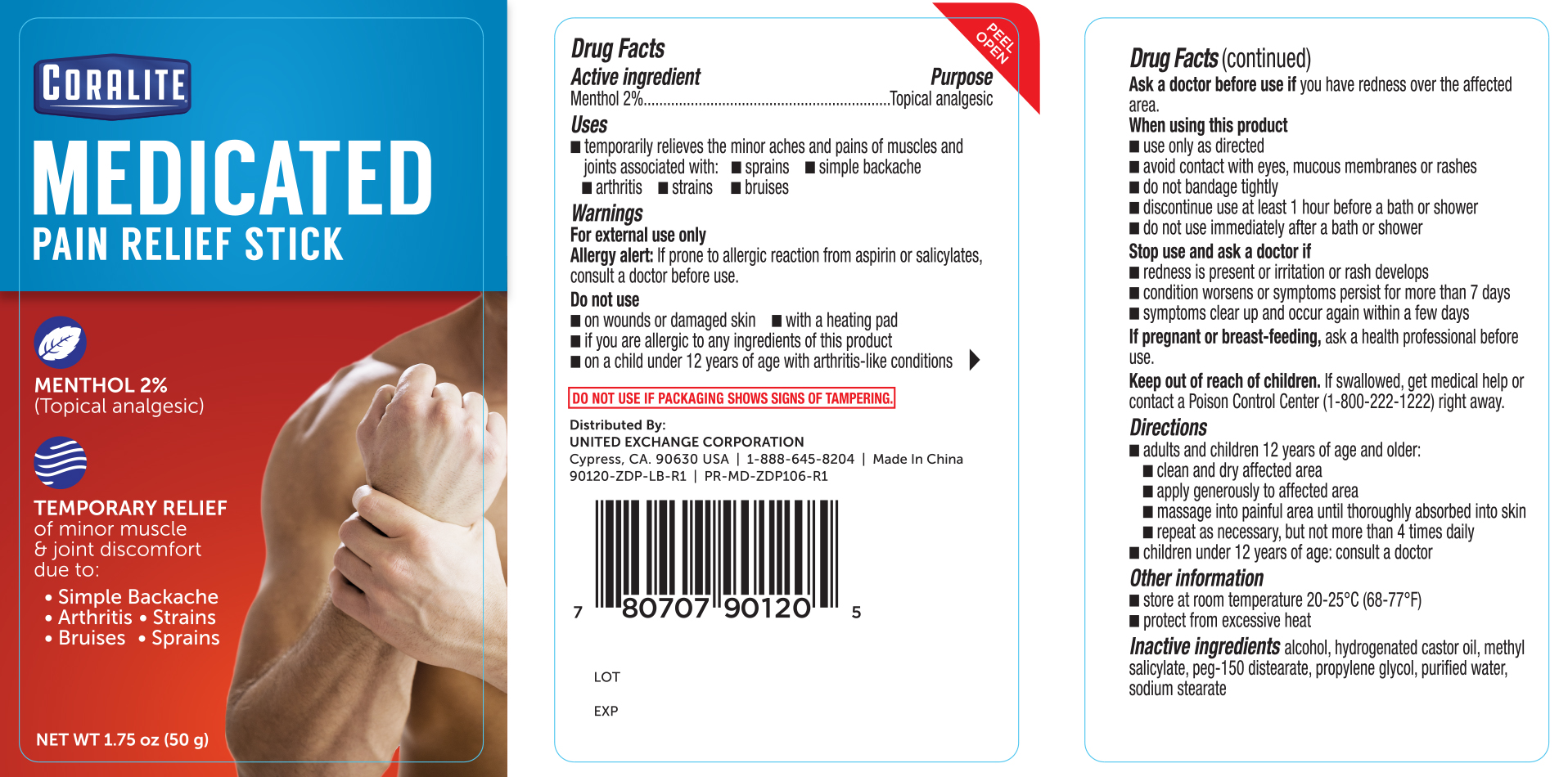 DRUG LABEL: Family Care Pain Relief
NDC: 65923-119 | Form: STICK
Manufacturer: United Exchange Corporation
Category: otc | Type: HUMAN OTC DRUG LABEL
Date: 20181030

ACTIVE INGREDIENTS: MENTHOL 20 mg/1 g
INACTIVE INGREDIENTS: WATER; METHYL SALICYLATE; ALCOHOL; HYDROGENATED CASTOR OIL; PEG-150 DISTEARATE; PROPYLENE GLYCOL; SODIUM STEARATE

Coralite Pain Relief Stick 1.75oz (90120, 2018)

Active ingredient Purpose

Menthol 2%.........................Topical analgesic

Uses

- Temporarily relieves the minor aches and pains of muscles and joints associated with:
- sprains
- simple backache
- arthritis
- strains
- bruises

Warnings

For external use only

Allergy alert: If prone to allergic reaction from aspirin or slicylates, consult a doctor before use.

Do not use

- on wounds or damaged skin
- with a heating pad
- if you are allergic to any ingredients of this product
- on a child under 12 years of age with arthritis-like conditions

DOSAGE AND ADMINISTRATION

Distributed By:

UNITED EXCHANGE CORPORATION

Cypress, CA. 90630 USA | 1-888-645-8204 | Made in China

Ask a doctor before use if you have redness over the affected area.

When using this product

- use only as directed
- avoid contact with eyes, mucous membranes or rashes
- do not bandage tightly
- discontinue use at least 1 hour before a bath or shower
- do not use immediately after a bath or shower

Stop use and ask a doctor if

- redness is present or irritation or rash develops
- condition worsens or symptoms persist for more than 7 days
- symptoms clear up and occur again within a few days

PREGNANCY OR BREAST FEEDING

If pregnant or breast-feeding, ask a health professional before use.

Keep out of reach of children. If swallowed, get medical help or contact a Poison Control Center (1-800-222-1222) right away.

Directions

- adults and children 12 years of age and older:
- clean and dry affected area
- apply generously to affected area
- massage into painful area until thoroughly absorbed into skin
- repeat as necessary, but not more than 4 times daily
- children under 12 years of age: consult a doctor

STORAGE AND HANDLING

- store at room temperature 20-25°C (68-77°F)
- protect from excessive heat

INACTIVE INGREDIENT

Inactive ingredients alcohol, hydrogenated castor oil, methyl salicylate, peg-150 distearate, propylene glycol, purified water, sodium stearate